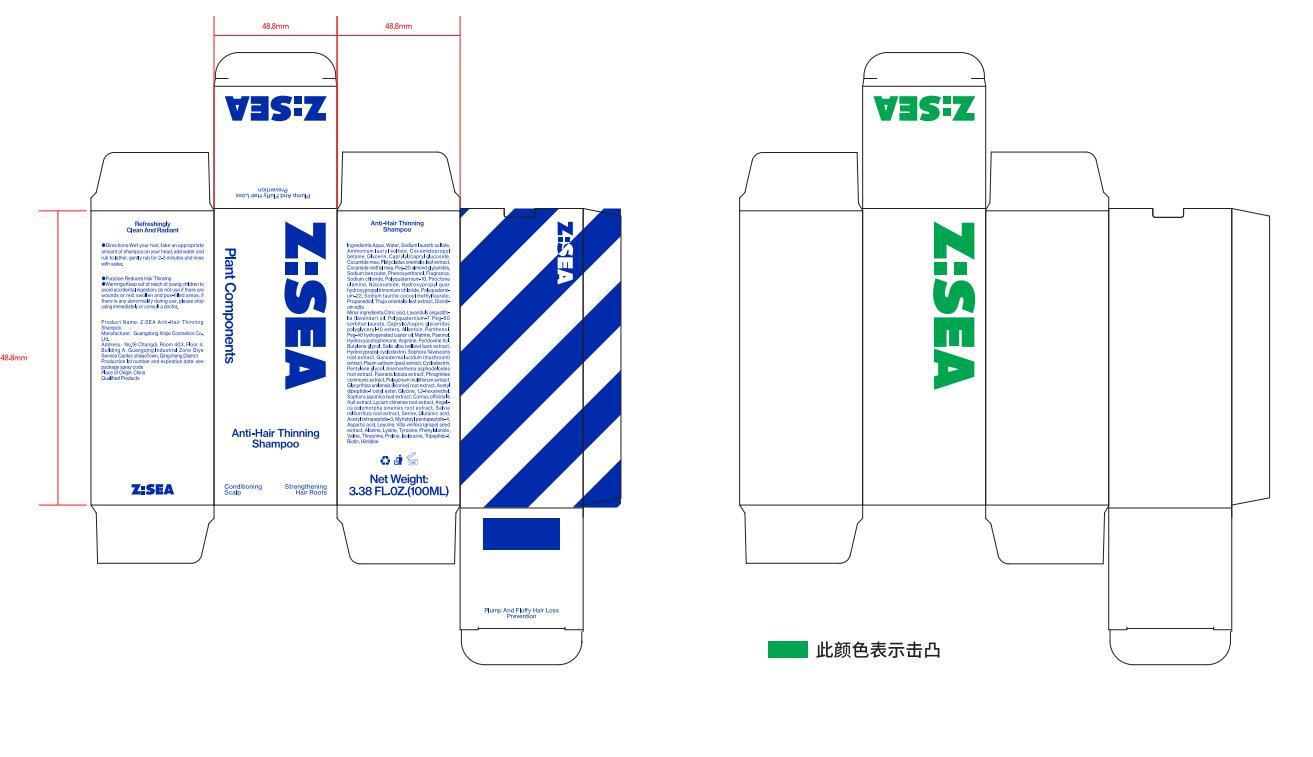 DRUG LABEL: Anti-Hair Thinning
NDC: 85769-123 | Form: SHAMPOO
Manufacturer: Guangdong Xinjie Cosmetics Co.,Ltd.
Category: homeopathic | Type: HUMAN OTC DRUG LABEL
Date: 20250603

ACTIVE INGREDIENTS: COCAMIDOPROPYL BETAINE 1.5 mg/1 mL
INACTIVE INGREDIENTS: 3-CHLORO-6-HYDROXYACETOPHENONE; HISTIDINE; CYCLODEXTRIN; PHENOXYETHANOL; LYSINE; 3-ISOPROPYLAMINO-1,2-PROPANEDIOL; 1,2-HEXANEDIOL; MYRISTOYL PENTAPEPTIDE-4; FRAGRANCE 13576; TRIPEPTIDE-1; BIOTIN; LAVANDULA ANGUSTIFOLIA (LAVENDER) OIL; ALLANTOIN; GLUTAMIC ACID; BUTYLENE GLYCOL; SODIUM CHLORIDE; GLYCINE; THREONINE; PROLINE; SODIUM LAURETH SULFATE; PAEONOL; AQUA; POLYQUATERNIUM-22 (6300 MPA.S); ASPARTIC ACID; TYROSINE; SODIUM BENZOATE; ISOLEUCINE; ACETYL DIPEPTIDE-1 CETYL ESTER; ACETYL TETRAPEPTIDE-3; PIROCTONE OLAMINE; CAPRYLYL/CAPRYL GLUCOSIDE; MAGNESIUM DISODIUM EDTA; COCAMIDE METHYL MEA; GLYCERIN; PEG-40 HYDROGENATED CASTOR OIL; HYDROXYPROPYL GUAR HYDROXYPROPYLTRIMONIUM CHLORIDE; MATRINE; 3-METHYLAMINO-4-NITROPHENOXYETHANOL; PYRIDOXINE HCL; SERINE; VALINE, D-; ALANINE; POLYQUATERNIUM-7; AMMONIUM LAURYL SULFATE; COCAMIDE MEA; ARGININE; PHENYLALANINE; NIACINAMIDE; PEG-80 SORBITAN LAURATE; LEUCINE

INACTIVE INGREDIENT

WATER,AQUA,SODIUM CHLORIDE,CAPRYLYL/CAPRYL GLUCOSIDE,GLYCERIN,COCAMIDE MEA,PLATYCLADUS ORIENTALIS LEAF EXTRACT,COCAMIDE METHYL MEA,PROPANEDIOL,PEG-40 HYDROGENATED CASTOR OIL,DISODIUM EDTA,HYDROXYACETOPHENONE,PEG-20 ALMOND GLYCERIDES,POLYQUATERNIUM-7SODIUM BENZOATE,PHENOXYETHANOL,SODIUM BENZOATE,POLYQUATERNIUM-22,FRAGRANCE,HYDROXYPROPYL GUAR HYDROXYPROPYLTRIMONIUM CHLORIDE,POLYQUATERNIUM-10,PIROCTONE OLAMINE,NIACINAMIDE,PEG-80 SORBITAN LAURATE,CAPRYLIC/CAPRIC GLYCERIDES POLYGLYCERYL-10 ESTERS,MATRINE,PAEONOL,SALIX ALBA (WILLOW) BARK EXTRACT,LAVANDULA ANGUSTIFOLIA (LAVENDER) OIL,ALLANTOIN,PANTHENOL,PEG-40 HYDROGENATED CASTOR OIL,ACETYL DIPEPTIDE-1 CETYL ESTER,BIOTIN,SOPHORA JAPONICA BUD EXTRACT,PUERARIA LOBATA EXTRACT,ANEMARRHENA ASPHODELOIDES ROOT EXTRACT,CYCLODEXTRIN,PISUM SATIVUM (PEA) EXTRACT,VITIS VINIFERA (GRAPE) SEED EXTRACT,CORNUS OFFICINALIS FRUIT EXTRACT,ANGELICA POLYMORPHA SINENSIS ROOT EXTRACT,PHRAGMITES COMMUNIS EXTRACT,POLYGONUM MULTIFLORUM EXTRACT

DOSAGE AND ADMINISTRATION

Net Weight:3.38 FL.OZ.(100ML)

WARNINGS

Keep out of reach of young children to avoid accidental ingestion

INDICATIONS AND USAGE

Wet your hair,take an approprtate amount of shampoo on your head, add water and rub to lather,gently rub for 2-3 minutes and rinse with water.

Keep out of reach of children section

PURPOSE

Reduces Hair Thinning

ACTIVE INGREDIENT

SODIUM LAURETH SULFATE,COCAMIDOPROPYL BETAINE,AMMONIUM LAURYL SULFATE